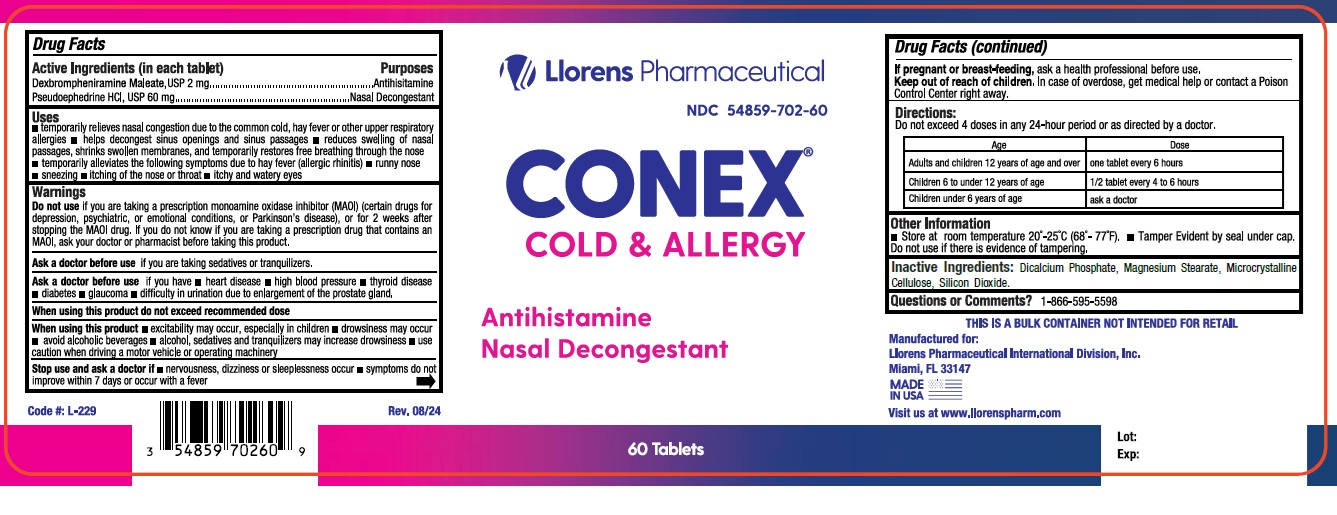 DRUG LABEL: Conex
NDC: 54859-702 | Form: TABLET
Manufacturer: LLORENS PHARMACEUTICALS INTERNATIONAL DIVISION
Category: otc | Type: HUMAN OTC DRUG LABEL
Date: 20251230

ACTIVE INGREDIENTS: DEXBROMPHENIRAMINE MALEATE 2 mg/1 1; PSEUDOEPHEDRINE HYDROCHLORIDE 60 mg/1 1
INACTIVE INGREDIENTS: CALCIUM PHOSPHATE, DIBASIC, ANHYDROUS; CELLULOSE, MICROCRYSTALLINE; MAGNESIUM STEARATE; SODIUM STARCH GLYCOLATE TYPE B POTATO; WATER; FERRIC OXIDE RED; FERRIC OXIDE YELLOW; TITANIUM DIOXIDE

Conex Tab Allergy 702

Active Ingredients (in each film coated tablet) Purpose

Dexbrompheniramine Maleate, USP ................ 2 mg .................. Antihistamine

Pseudeophedrine HCl, USP .................... 60 mg ..........................Nasal Decogestant

Uses

- Temporarily relieves nasal congestion due to the common cold, hay fever or other upper respiratory allergies
- helps decongest sinus openings and sinus passages
- Reduces swelling of nasal passages, shrinks swollen membranes, and temporarily restores freer breathing through the nose
- Temporarily alleviates the following symptoms due to hay fever (allergic rhinitis): runny nose, sneezing, itching of the nose or throat, itching and watery eyes.

Warnings:

Ask a doctor before you use if you are

- taking sedatives or tranquilizers.

Ask your doctor before use if you have

- heart disease
- high blood pressure
- thyroid disease
- diabetes
- glaucoma
- difficulty in urination due to the enlargement of the prostate gland.

When using this product

- do not exceed the recommended dosage
- excitability may occur, especially in children
- drowsiness may occur
- avoid alcoholic beverages
- alcohol, sedatives and tranquilizers may increase drowsiness
- use caution when driving a motor vehicle or operating machinery

Stop use and ask doctor if

- nervousness, dizziness or sleepiness occur
- symptoms do not improve withing 7 days or occur with a fever

KEEP OUT OF REACH OF CHILDREN

Keep out of the reach of children.In case of overdose, get medical help or contact a Poison Control Center right away.

PREGNANCY OR BREAST FEEDING

If pregnant or breast-feeding,ask a health professional before use.

DO NOT USE

Do not useif you are taking a prescription monoamine oxidase inhibitor (MAOI) (certain drugs for depression, psychiatric, or emotional conditions

or Parkinson's disease), or for 2 weeks after stopping the MAOI drug. If you do not know if you are taking a prescription drug that contains MAOI;

ask your doctor or pharmacist before taking this product.

DOSAGE AND ADMINISTRATION

Directions:Do not exceed more than 4 tablets in any 24-hour period or as directed by a doctor.

Adults and children 12 years of age and over | Take one tablet every 6 hours
Children 6 to under 12 years of age | 1/2 tablet every 4 to 6 hours
Children under 6 years of age | Ask a doctor

Other Information:Store at controlled room temperature 20 - 25 degree celsius (68 - 77 degree fahrenheit); excursions permitted to

15 - 30 degree celsius (59 - 86 degree fahrenheit) [ See USP Controlled Room Temperature] Tamper evident by imprinted heat seal

under cap. Do not use if there is evidence of tampering.

INACTIVE INGREDIENT

Inactive Ingredients:Dicalcium Phosphate, Microcrystalline Cellulose, Magnesium Stearate, Silicon dioxide

Questions or Comments? 1-866-595-5598

RECENT MAJOR CHANGES

Fixed typographical error in Dosification directions